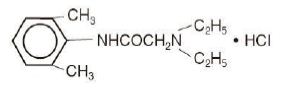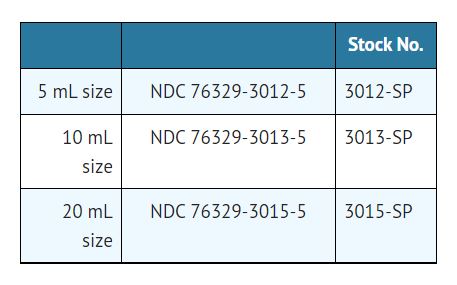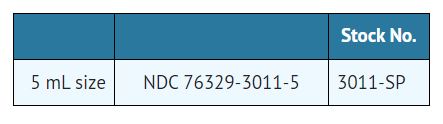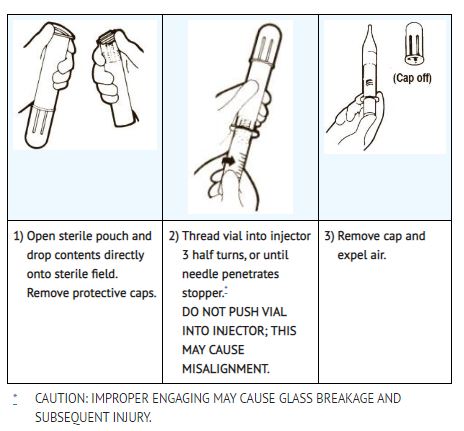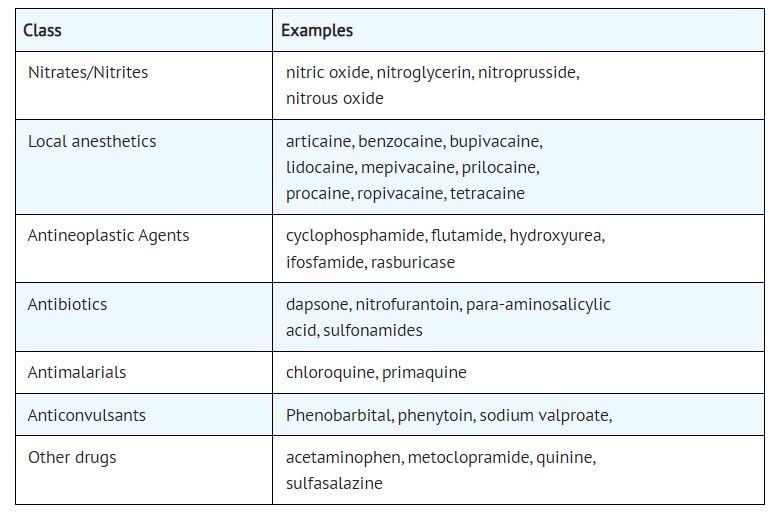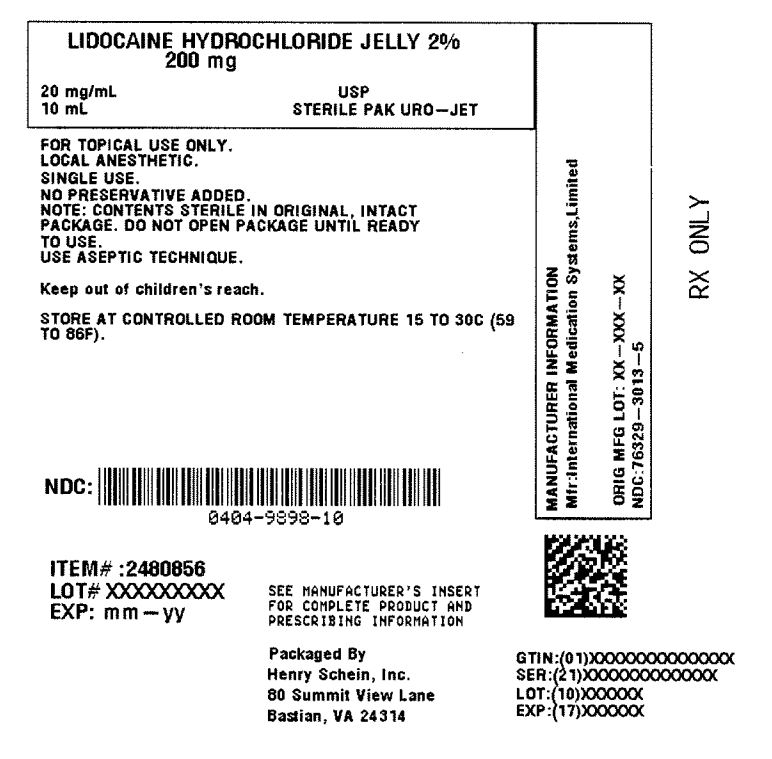 DRUG LABEL: Lidocaine Hydrochloride
NDC: 0404-9898 | Form: JELLY
Manufacturer: Henry Schein, Inc.
Category: prescription | Type: HUMAN PRESCRIPTION DRUG LABEL
Date: 20251031

ACTIVE INGREDIENTS: Lidocaine Hydrochloride 20 mg/1 mL

LIDOCAINE HYDROCHLORIDE JELLY USP, 2% A STERILE, WATER-SOLUBLE, TOPICAL ANESTHETIC

DESCRIPTION

Lidocaine Hydrochloride Jelly USP, 2% is a sterile aqueous product that contains a local anesthetic agent and is administered topically (see INDICATIONS AND USAGE for specific uses).

Lidocaine Hydrochloride Jelly USP, 2% contains lidocaine hydrochloride which is chemically designated as acetamide, 2-(diethylamino)-N-(2,6-dimethylphenyl)-, monohydrochloride and has the following structural formula:

Lidocaine Hydrochloride Jelly USP, 2% also contains sodium carboxymethylcellulose, and the resulting mixture maximizes contact with mucosa and provides lubrication for instrumentation. The unused portion should be discarded after initial use.

Composition of Lidocaine Hydrochloride Jelly USP, 2%: Each mL contains 20 mg of lidocaine HCI. The formulation also contains sodium carboxymethylcellulose and sodium hydroxide and/or hydrochloric acid to adjust pH between 6.0 to 7.0.

CLINICAL PHARMACOLOGY:

Mechanism of action
Lidocaine stabilizes the neuronal membrane by inhibiting the ionic fluxes required for the initiation and conduction of impulses, thereby effecting local anesthetic action.

Onset of action
The onset of action is 3 to 5 minutes. It is ineffective when applied to intact skin.

Hemodynamics
Excessive blood levels may cause changes in cardiac output, total peripheral resistance, and mean arterial pressure. These changes may be attributable to a direct depressant effect of the local anesthetic agent on various components of the cardiovascular system.

Pharmacokinetics and Metabolism
Lidocaine may be absorbed following topical administration to mucous membranes, its rate and extent of absorption varies depending upon concentration and total dose administered, the specific site of application, and duration of exposure. In general, the rate of absorption of local anesthetic agents following topical application occurs most rapidly after intratracheal administration. Lidocaine is also well-absorbed from the gastrointestinal tract, but little intact drug may appear in the circulation because of biotransformation in the liver.

Lidocaine is metabolized rapidly by the liver, and metabolites and unchanged drug are excreted by the kidneys. Biotransformation includes oxidative N-dealkylation, ring hydroxylation, cleavage of the amide linkage, and conjugation. N-dealkylation, a major pathway of biotransformation, yields the metabolites monoethylglycinexylidide and glycinexylidide. The pharmacological / toxicological actions of these metabolites are similar to, but less potent than, those of lidocaine. Approximately 90% of lidocaine administered is excreted in the form of various metabolites, and less than 10% is excreted unchanged.

The primary metabolite in urine is a conjugate of 4-hydroxy-2, 6-dimethylaniline.

The plasma binding of lidocaine is dependent on drug concentration, and the fraction bound decreases with increasing concentration. At concentrations of 1 to 4 mcg of free base per mL, 60 to 80 percent of lidocaine is protein bound. Binding is also dependent on the plasma concentration of the alpha-1-acid glycoprotein.

Lidocaine crosses the blood-brain and placental barriers, presumably by passive diffusion.

Studies of lidocaine metabolism following intravenous bolus injections have shown that the elimination half-life of this agent is typically 1.5 to 2 hours. Because of the rapid rate at which lidocaine is metabolized, any condition that affects liver function may alter lidocaine kinetics. The half-life may be prolonged twofold or more in patients with liver dysfunction. Renal dysfunction does not affect lidocaine kinetics but may increase the accumulation of metabolites.

Factors such as acidosis and the use of CNS stimulants and depressants affect the CNS levels of lidocaine required to produce overt systemic effects. Objective adverse manifestations become increasingly apparent with increasing venous plasma levels above 6 mcg free base per mL. In the rhesus monkey arterial blood levels of 18 to 21 mcg/mL have been shown to be the threshold for convulsive activity.

INDICATIONS & USAGE:

Lidocaine Hydrochloride Jelly USP, 2% is indicated for prevention and control of pain in procedures involving the male and female urethra for topical treatment of painful urethritis, and as an anesthetic lubricant for endotracheal intubation (oral and nasal).

CONTRAINDICATIONS:

Lidocaine is contraindicated in patients with a known history of hypersensitivity to local anesthetics of the amide type or to other components of Lidocaine Hydrochloride Jelly USP, 2%.

WARNINGS:

EXCESSIVE DOSAGE, OR SHORT INTERVALS BETWEEN DOSES, CAN RESULT IN HIGH PLASMA LEVELS AND SERIOUS ADVERSE EFFECTS. PATIENTS SHOULD BE INSTRUCTED TO STRICTLY ADHERE TO THE RECOMMENDED DOSAGE AND ADMINISTRATION GUIDELINES AS SET FORTH IN THIS PACKAGE INSERT. THE MANAGEMENT OF SERIOUS ADVERSE REACTIONS MAY REQUIRE THE USE OF RESUSCITATIVE EQUIPMENT, OXYGEN, AND OTHER RESUSCITATIVE DRUGS.

Lidocaine Hydrochloride Jelly USP, 2% should be used with extreme caution in the presence of sepsis or severely traumatized mucosa in the area of application, since under such conditions there is the potential for rapid systemic absorption.
When used for endotracheal tube lubrication, care should be taken to avoid introducing the product into the lumen of the tube. Do not use the jelly to lubricate the endotracheal stylettes. lf allowed into the inner lumen, the jelly may dry on the inner surface leaving a residue which tends to clump with flexion, narrowing the lumen. There have been rare reports in which this residue has caused the lumen to occlude (see ADVERSE REACTIONS and DOSAGE AND ADMINISTRATION).

Methemoglobinemia
Cases of methemoglobinemia have been reported in association with local anesthetic use. Although all patients are at risk for methemoglobinemia, patients with glucose-6-phosphate dehydrogenase deficiency, congenital or idiopathic methemoglobinemia, cardiac or pulmonary compromise, infants under 6 months of age, and concurrent exposure to oxidizing agents or their metabolites are more susceptible to developing clinical manifestations of the condition. If local anesthetics must be used in these patients, close monitoring for symptoms and signs of methemoglobinemia is recommended.

Signs of methemoglobinemia may occur immediately or may be delayed some hours after exposure, and are characterized by a cyanotic skin discoloration and/or abnormal coloration of the blood. Methemoglobin levels may continue to rise; therefore, immediate treatment is required to avert more serious central nervous system and cardiovascular adverse effects, including seizures, coma, arrhythmias, and death. Discontinue Lidocaine Hydrochloride Jelly USP, 2% and any other oxidizing agents. Depending on the severity of the signs and symptoms, patients may respond to supportive care, i.e., oxygen therapy, hydration. A more severe clinical presentation may require treatment with methylene blue, exchange transfusion, or hyperbaric oxygen.

PRECAUTIONS:

General
The safety and effectiveness of lidocaine depend on proper dosage, correct technique, adequate precautions, and readiness for emergencies (see WARNINGS and ADVERSE REACTIONS). The lowest dosage that results in effective anesthesia should be used to avoid high plasma levels and serious adverse effects. Repeated doses of lidocaine may cause significant increases in blood levels with each repeated dose because of slow accumulation of the drug or its metabolites. Tolerance to elevated blood levels varies with the status of the patient. Debilitated, elderly patients, acutely ill patients, and children should be given reduced doses commensurate with their age and physical status. Lidocaine should also be used with caution in patients with severe shock or heart block.

Lidocaine Hydrochloride Jelly USP, 2% should be used with caution in patients with known drug sensitivities. Patients allergic to para-aminobenzoic acid derivatives (procaine, tetracaine, benzocaine, etc.) have not shown cross sensitivity to lidocaine.

Many drugs used during the conduct of anesthesia are considered potential triggering agents for familial malignant hyperthermia. Since it is not known whether amide-type local anesthetics may trigger this reaction and since the need for supplemental general anesthesia cannot be predicted in advance, it is suggested that a standard protocol for management should be available. Early unexplained signs of tachycardia, tachypnea, labile blood pressure and metabolic acidosis may precede temperature elevation. Successful outcome is dependent on early diagnosis, prompt discontinuance of the suspect triggering agent(s) and institution of treatment, including oxygen therapy, indicated supportive measures and dantrolene (consult dantrolene sodium intravenous package insert before using).

Information for Patients
Inform patients that use of local anesthetics may cause methemoglobinemia, a serious condition that must be treated promptly. Advise patients or caregivers to seek immediate medical attention if they or someone in their care experience the following signs or symptoms: pale, gray, or blue colored skin (cyanosis); headache; rapid heart rate; shortness of breath; lightheadedness; or fatigue.

When topical anesthetics are used in the mouth, the patient should be aware that the production of topical anesthesia may impair swallowing and thus enhance the danger of aspiration. For this reason, food should not be ingested for 60 minutes following use of local anesthetic preparations in the mouth or throat area. This is particularly important in children because of their frequency of eating.

Numbness of the tongue or buccal mucosa may enhance the danger of unintentional biting trauma. Food and chewing gum should not be taken while the mouth or throat area is anesthetized.

Drug Interactions
Patients who are administered local anesthetics are at increased risk of developing methemoglobinemia when concurrently exposed to the following drugs, which could include other local anesthetics:

Examples of Drugs Associated with Methemoglobinemia:

Carcinogenesis Long-term studies in animals have not been performed to evaluate the carcinogenic potential of lidocaine.

Mutagenesis
The mutagenic potential of lidocaine has been tested in the Ames Salmonella reverse mutation assay, an in vitro chromosome aberrations assay in human lymphocytes and in an in vivo mouse micronucleus assay. There was no indication of any mutagenic effect in these studies.

Impairment of Fertility
The effect of lidocaine on fertility was examined in the rat model. Administration of 30 mg/kg, s.c. (180 mg/m^2) to the mating pair did not produce alterations in fertility or general reproductive performance of rats. There are no studies that examine the effect of lidocaine on sperm parameters. There was no evidence of altered fertility.

Use in Pregnancy
Teratogenic Effects
Teratogenic Effects: Pregnancy Category B.
Reproduction studies for lidocaine have been performed in both rats and rabbits. There was no evidence of harm to the fetus at subcutaneous doses of up to 50 mg/kg lidocaine (300 mg/m^2 on a body surface area basis) in the rat model. In the rabbit model, there was no evidence of harm to the fetus at a dose of 5 mg/kg, s.c. (60 mg/m^2 on a body surface area basis). Treatment of rabbits with 25 mg/kg (300 mg/m^2) produced evidence of maternal toxicity and evidence of delayed fetal development, including a non-significant decrease in fetal weight (7%) and an increase in minor skeletal anomalies (skull and sternebral defect, reduced ossification of the phalanges). The effect of lidocaine on post-natal development was examined in rats by treating pregnant female rats daily subcutaneously at doses of 2, 10, and 50 mg/kg (12, 60, and 300 mg/m^2) from day 15 of pregnancy and up to 20 days post partum. No signs of adverse effects were seen either in dams or in the pups up to and including the dose of 10 mg/kg (60 mg/m^2); however, the number of surviving pups was reduced at 50 mg/kg (300 mg/m^2), both at birth and the duration of lactation period, the effect most likely being secondary to maternal toxicity. No other effects on litter size, litter weight, abnormalities in the pups and physical developments of the pups were seen in this study.

A second study examined the effects of lidocaine on post-natal development in the rat that included assessment of the pups from weaning to sexual maturity. Rats were treated for 8 months with 10 or 30 mg/kg, s.c. lidocaine (60 mg/m^2 and 180 mg/m^2 on a body surface area basis, respectively). This time period encompassed 3 mating periods. There was no evidence of altered post-natal development in any offspring; however, both doses of lidocaine significantly reduced the average number of pups per litter surviving until weaning of offspring from the first 2 mating period.

There are, however, no adequate and well-controlled studies in pregnant women. Because animal reproduction studies are not always predictive of human response, this drug should be used during pregnancy only if clearly needed.

Labor and Delivery
Lidocaine is not contraindicated in labor and delivery. Should Lidocaine Hydrochloride Jelly USP, 2% be used concomitantly with other products containing lidocaine, the total dose contributed by all formulations must be kept in mind.

Nursing Mothers
Lidocaine is secreted in human milk. The clinical significance of this observation is unknown. Caution should be exercised when lidocaine is administered to a nursing woman.

Pediatric Use
Although, the safety and effectiveness of Lidocaine Hydrochloride Jelly USP, 2% in pediatric patients have not been established, a study of 19 premature neonates (gestational age <33 weeks) found no correlation between the plasma concentration of lidocaine or monoethylglycinexylidide and infant body weight when moderate amounts of lidocaine (i.e. 0.3 mL/kg of lidocaine gel 20 mg/ml) were used for lubricating both intranasal and endotracheal tubes. No neonate had plasma levels of lidocaine above 750 mcg/L. Dosages in children should be reduced, commensurate with age, body weight, and physical condition. (See DOSAGE AND ADMINISTRATION.)

ADVERSE REACTIONS:

Adverse experiences following the administration of lidocaine are similar in nature to those observed with other amide local anesthetic agents. These adverse experiences are, in general, dose-related and may result from high plasma levels caused by excessive dosage or rapid absorption, or may result from a hypersensitivity, idiosyncrasy, or diminished tolerance on the part of the patient. Serious adverse experiences are generally systemic in nature. The following types are those most commonly reported:

There have been rare reports of endotracheal tube occlusion associated with the presence of dried jelly residue in the inner lumen of the tube (see WARNINGS and DOSAGE AND ADMINISTRATION).

Central Nervous System
CNS manifestations are excitatory and/or depressant and may be characterized by lightheadedness, nervousness, apprehension, euphoria, confusion, dizziness, drowsiness, tinnitus, blurred or double vision, vomiting, sensations of heat, cold or numbness, twitching, tremors, convulsions, unconsciousness, respiratory depression and arrest. The excitatory manifestations may be very brief or may not occur at all, in which case the first manifestation of toxicity may be drowsiness merging into unconsciousness and respiratory arrest.

Drowsiness following the administration of lidocaine is usually an early sign of a high blood level of the drug and may occur as a consequence of rapid absorption.

Cardiovascular system
Cardiovascular manifestations are usually depressant and are characterized by bradycardia, hypotension, and cardiovascular collapse, which may lead to cardiac arrest.

Allergic
Allergic reactions are characterized by cutaneous lesions, urticaria, edema or anaphylactoid reactions. Allergic reactions may occur as a result of sensitivity either to the local anesthetic agent or to other components in the formulation. Allergic reactions as a result of sensitivity to lidocaine are extremely rare and, if they occur, should be managed by conventional means. The detection of sensitivity by skin testing is of doubtful value.

DOSAGE AND ADMINISTRATION:

When Lidocaine Hydrochloride Jelly USP, 2% is used concomitantly with other products containing lidocaine, the total dose contributed by all formulations must be kept in mind.

The dosage varies and depends upon the area to be anesthetized, vascularity of the tissues, individual tolerance, and the technique of anesthesia. The lowest dosage needed to provide effective anesthesia should be administered. Dosages should be reduced for children and for elderly and debilitated patients. Although the incidence of adverse effects with Lidocaine Hydrochloride Jelly USP, 2% is quite low, caution should be exercised, particularly when employing large amounts, since the incidence of adverse effects is directly proportional to the total dose of local anesthetic agent administered.

For Surface Anesthesia of the Male Adult Urethra
Slowly instill approximately 15 mL (300 mg of lidocaine HCl) into the urethra or until the patient has a feeling of tension. A penile clamp is then applied for several minutes at the corona. An additional dose of not more than 15 mL (300 mg) can be instilled for adequate
anesthesia.

Prior to sounding or cystoscopy, a penile clamp should be applied for 5 to 10 minutes to obtain adequate anesthesia. A total dose of 30 mL (600 mg) is usually required to fill and dilate the male urethra. Prior to catheterization, smaller volumes of 5 to 10 mL (100 to 200 mg) are usually adequate for lubrication.

For Surface Anesthesia of the Female Adult Urethra
Slowly instill 3 to 5 mL (60 to 100 mg of lidocaine HCl) of the jelly into the urethra. If desired, some jelly may be deposited on a cotton swab and introduced into the urethra. In order to obtain adequate anesthesia, several minutes should be allowed prior to performing urological procedures.

Lubrication for Endotracheal Intubation
Apply a moderate amount of jelly to the external surface of the endotracheal tube shortly before use. Care should be taken to avoid introducing the product into the lumen of the tube. Do not use the jelly to lubricate endotracheal stylettes. See WARNINGS and ADVERSE REACTIONS concerning rare reports of inner lumen occlusion. It is also recommended that use of endotracheal tubes with dried jelly on the external surface be avoided for lack of lubricating effect.

MAXIMUM DOSAGE:
No more than 600 mg of lidocaine hydrochloride should be given in any 12 hour period.

Children
It is difficult to recommend a maximum dose of any drug for children since this varies as a function of age and weight. For children less than ten years who have a normal lean body mass and a normal lean body development, the maximum dose may be determined by the application of one of the standard pediatric drug formulas (e.g., Clark's rule). For example, in a child of five years weighing 50 lbs., the dose of lidocaine hydrochloride should not exceed 75–100 mg when calculated according to Clark's rule. In any case, the maximum amount of lidocaine administered should not exceed 4.5 mg / kg (2 mg / lb) of body weight.

Overdosage

Acute emergencies from local anesthetics are generally related to high plasma levels encountered during therapeutic use of local anesthetics. (See ADVERSE REACTIONS, WARNINGS, and PRECAUTIONS.)

Management of local anesthetic emergencies
The first consideration is prevention, best accomplished by careful and constant monitoring of cardiovascular and respiratory vital signs and the patient's state of consciousness after each local anesthetic administration. At the first sign of change, oxygen should be administered.

The first step in the management of convulsions consists of immediate attention to the maintenance of a patent airway and assisted or controlled ventilation with oxygen and a delivery system capable of permitting immediate positive airway pressure by mask. Immediately after the institution of these ventilatory measures, the adequacy of the circulation should be evaluated, keeping in mind that drugs used to treat convulsions sometimes depress the circulation when administered intravenously. Should convulsions persist despite adequate respiratory support and if the status of the circulation permits, small increments of an ultra-short acting barbiturate (such as thiopental or thiamylal) or a benzodiazepine (such as diazepam) may be administered intravenously. The clinician should be familiar, prior to use of local anesthetics, with these anticonvulsant drugs. Supportive treatment of circulatory depression may require administration of intravenous fluids and when appropriate, a vasopressor as directed by the clinical situation (e.g. ephedrine).

If not treated immediately, both convulsions and cardiovascular depression can result in hypoxia, acidosis, bradycardia, arrhythmias and cardiac arrest. If cardiac arrest should occur, standard cardiopulmonary resuscitative measures should be instituted.

Dialysis is of negligible value in the treatment of acute overdosage with lidocaine.

The oral LD50 of lidocaine hydrochloride in non-fasted female rats is 459 (346–773) mg / kg (as the salt) and 214 (159–324) mg / kg (as the salt) in fasted female rats.

HOW SUPPLIED:

Lidocaine Hydrochloride Jelly USP, 2%

Box of 25

In unit use packages containing one single use vial and a URO-JET® vial injector.

In unit use packages containing one single use vial and a URO-JET® AC (Anatomically Constricted) vial injector.

Box of 25

Syringe Assembly Directions
Syringe Assembly Directions:
USE ASEPTIC TECHNlQUE
Do not assemble until ready to use.

Store at controlled room temperature 15° to 30°C (59° to 86°F).

Rx Only

Product repackaged by: Henry Schein, Inc., Bastian, VA 24314
From Original Manufacturer/Distributor's NDC and Unit of Sale | To Henry Schein Repackaged Product NDC and Unit of Sale | Total Strength/Total Volume (Concentration) per unit
NDC 76329-3012-5 Box of 25 In unit use packages containing one single use vial and a URO-JET® vial injector | NDC 0404-9900-05 1 unit use package containing 1 5 mL single use vial and a URO-JET® vial injector in a bag (Vial bears NDC 76329-3012-5) | 2%
NDC 76329-3013-5 Box of 25 In unit use packages containing one single use vial and a URO-JET® vial injector | NDC 0404-9898-10 1 unit use package containing 1 10 mL single use vial and a URO-JET® vial injector in a bag (Vial bears 76329-3013-5) | 2%
NDC 76329-3015-5 Box of 25 In unit use packages containing one single use vial and a URO-JET® vial injector | NDC 0404-9899-20 1 unit use package containing 1 20 mL single use vial and a URO-JET® vial injector in a bag (Vial bears NDC 76329-3015-5) | 2%

SPL UNCLASSIFIED SECTION

INTERNATIONAL MEDICATION SYSTEMS, LIMITED

SOUTH EL MONTE, CA 91733, U.S.A.
An Amphastar Pharmaceuticals Company

REV. 8-24

6930120R